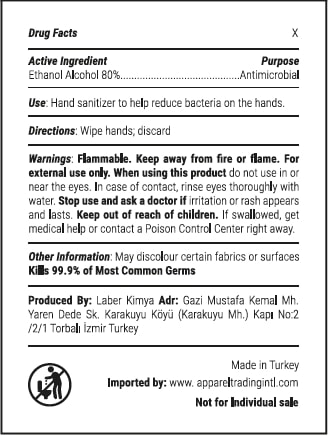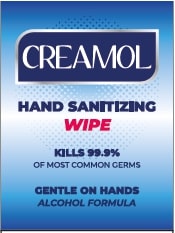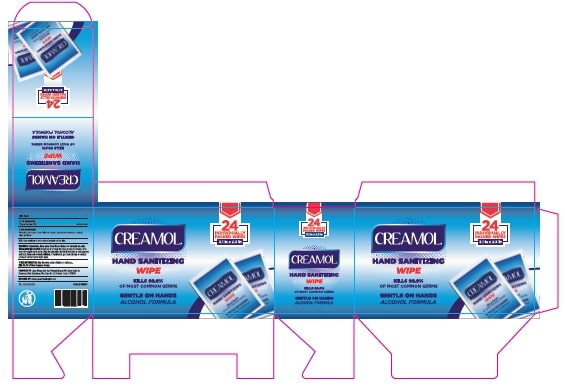 DRUG LABEL: Creamol Hand Sanitizer Wipe
NDC: 77892-0009 | Form: SWAB
Manufacturer: LABER KIMYA AR-GE SANAYI TICARET - LEVENT KAHRIMAN
Category: otc | Type: HUMAN OTC DRUG LABEL
Date: 20200907

ACTIVE INGREDIENTS: ALCOHOL 80 g/100 g
INACTIVE INGREDIENTS: HYPERICUM PERFORATUM; GLYCERIN; MELALEUCA ALTERNIFOLIA LEAF; WATER

CREAMOL HAND SANITIZING WIPE

ACTIVE INGREDIENT

Ethanol alcohol 80%. (w/w) Purpose: Antimicrobial

PURPOSE

Antiseptic, Hand Sanitizer

INDICATIONS AND USAGE

Hand Sanitizer to help reduce bacteria that potentially can cause disease. For use when soap and water are not available. Wipe hands; discard.

WARNINGS

For external use only. Flammable. Keep away from heat or flame

Do not use,

- in children less than 2 months of age
- on open skin wounds

When using this product keep out of eyes, ears, and mouth. In case of contact with eyes, rinse eyes thoroughly with water.
Stop use and ask a doctor if irritation or rash occurs. These may be signs of a serious condition.
Keep out of reach of children. If swallowed, get medical help or contact a Poison Control Center right away.

Stop use and ask a doctor if irritation or rash occurs. These may be signs of a serious condition.

Keep out of reach of children. If swallowed, get medical help or contact a Poison Control Center right away.

Directions

Wipe hands and dischard.

Other information

- Store between 15-30C (59-86F)
- Avoid freezing and excessive heat above 40C (104F)

INACTIVE INGREDIENT

glycerin, Hypericum perforatum, Melaleuca alternifolia, water, parfum